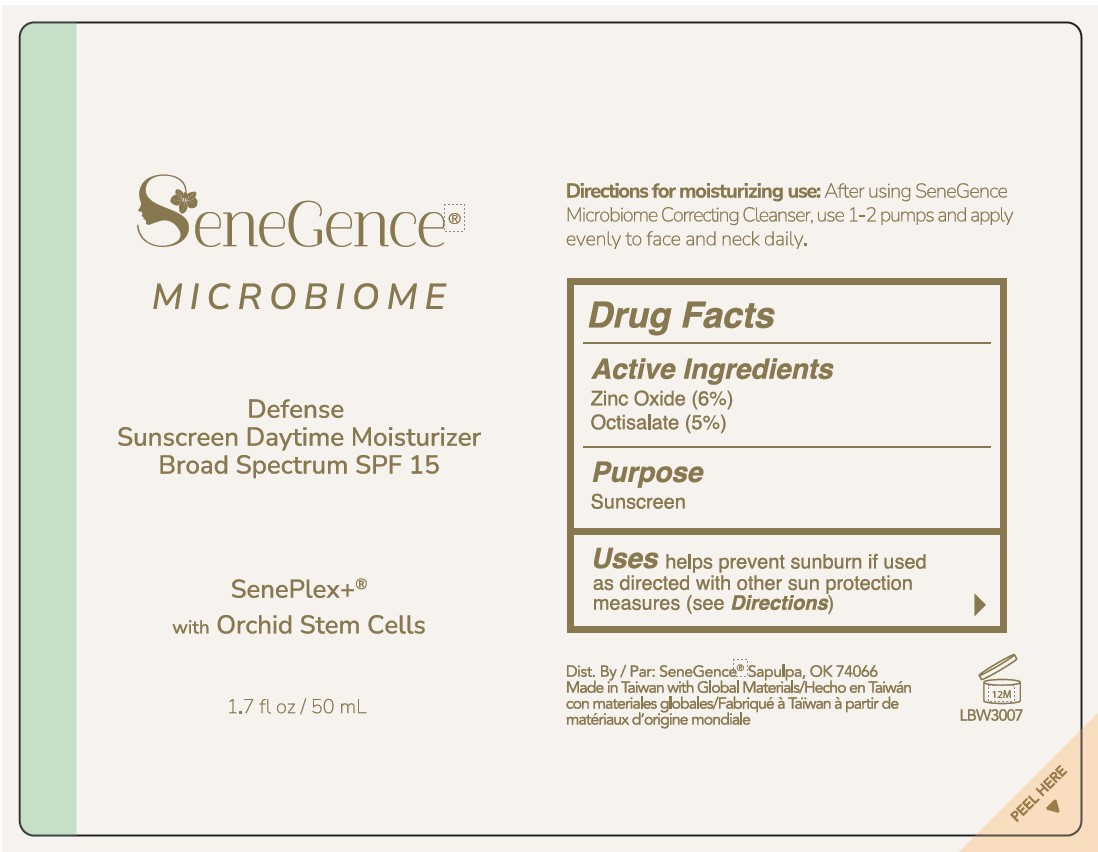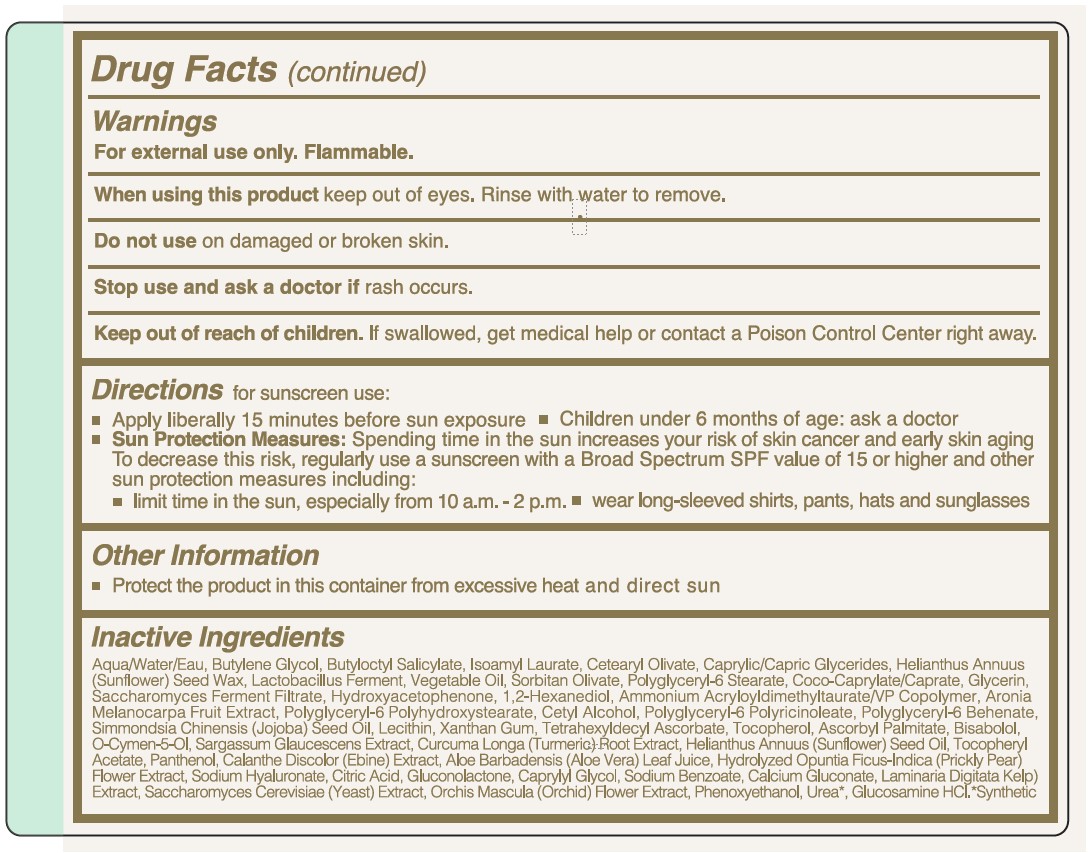 DRUG LABEL: SeneGence Microbiome Defense Sunscreen Daytime Moisturizer SPF15
NDC: 72644-638 | Form: LOTION
Manufacturer: SGII, INC
Category: otc | Type: HUMAN OTC DRUG LABEL
Date: 20240509

ACTIVE INGREDIENTS: OCTISALATE 5 g/100 mL; ZINC OXIDE 6 g/100 mL
INACTIVE INGREDIENTS: TURMERIC; .ALPHA.-TOCOPHEROL ACETATE; HYALURONATE SODIUM; CITRIC ACID MONOHYDRATE; GLUCONOLACTONE; ALOE VERA LEAF; CALCIUM GLUCONATE; ARONIA MELANOCARPA FRUIT; TOCOPHEROL; ORCHIS MASCULA FLOWER; LECITHIN, SOYBEAN; XANTHAN GUM; LEVOMENOL; SODIUM BENZOATE; PHENOXYETHANOL; POLYGLYCERYL-6 STEARATE; BUTYLOCTYL SALICYLATE; CORN OIL; SORBITAN OLIVATE; ASCORBYL PALMITATE; CETYL ALCOHOL; JOJOBA OIL; TETRAHEXYLDECYL ASCORBATE; O-CYMEN-5-OL; CAPRYLYL GLYCOL; 1,2-HEXANEDIOL; LIMOSILACTOBACILLUS FERMENTUM; CETEARYL OLIVATE; HELIANTHUS ANNUUS SEED WAX; COCO-CAPRYLATE/CAPRATE; POLYGLYCERYL-6 POLYRICINOLEATE; LAMINARIA DIGITATA; BUTYLENE GLYCOL; SUNFLOWER OIL; WATER; ISOAMYL LAURATE; POLYGLYCERYL-2 DIPOLYHYDROXYSTEARATE; UREA; POLYGLYCERYL-6 BEHENATE; SACCHAROMYCES CEREVISIAE; GLYCERIN; PEG-5 CAPRYLIC/CAPRIC GLYCERIDES; HYDROXYACETOPHENONE; AMMONIUM ACRYLOYLDIMETHYLTAURATE/VP COPOLYMER; PANTHENOL; OPUNTIA FICUS-INDICA FLOWER; GLUCOSAMINE HYDROCHLORIDE

SeneGence Microbiome Defense Sunscreen Daytime Moisturizer SPF15

Active Ingredients

Zinc Oxide (6%)

Octisalate (5%)

Purpose

Zinc Oxide (6%).............Sunscreen

Octisalate (5%)..............Sunscreen

Uses

helps prevent sunburn if used as directed with other sun protection measures (see Directions)

Warnings

For external use only. Flammable.

When using this product keep out of eyes. Rinse with water to remove.

Do not use on damaged or broken skin.

Stop use and ask a doctor if rash occurs.

Keep out of reach of children. If swallowed, get medical help or contact a Poison Control Center right away.

Directions

for sunscreen use:

- Apply liberally 15 minutes before sun exposure
- Children under 6 months of age: ask a doctor
- Sun Protection Measures: Spending time in the sun increases your skin cancer and early skin aging. To decrease this risk, regularly use a sunscreen with a Broad Spectrum SPF value of 15 or higher and other sun protection measures including:
- limit time in the sun, especially from 10 a.m.-2 p.m.
- wear long-sleeved shirts, pants, hats and sunglasses

Other Information

- Protect the product in this container from excessive heat and direct sun

Inactive Ingredients

Aqua/Water/Eau, Butylene Glycol, Butyloctyl Salicylate, Isoamyl Laurate, Cetearyl Olivate, Caprylic/Capric Glycerides, Helianthus Annuus (Sunflower) Seed Wax, Lactobacillus Ferment, Vegetable Oil, Sorbitan Olivate, Polyglyceryl-6 Stearate, Coco-Caprylate/Caprate, Glycerin, Saccharomyces Ferment Filtrate, Hydroxyacetophenone, 1,2-Hexanediol, Ammonium Acryloyldimethyltaurate/VP Copolymer, Aronia Melanocarpa Fruit Extract, Polyglyceryl-6 Polyhydroxystearate, Cetyl Alcohol, Polyglyceryl-6 Polyricinoleate, Polyglyceryl-6 Behenate, Simmondsia Chinensis (Jojoba) Seed Oil, Lecithin, Xanthan Gum, Tetrahexyldecyl AScorbate, Tocopherol, Ascorbyl Palmitate, Bisabolol, O-Cymen-5-Ol, Sargassum Glaucescens Extract, Curcuma Longa (Turmeric) Root Extract, Helianthus Annuus (Sunflower) Seed Oil, Tocopheryl Acetate, Panthenol, Calanthe Discolor (Ebine) Extract, Aloe Barbadensis (Aloe Vera) Leaf Juice, Hydrolyzed Opuntia Ficus-Indica (Prickly Pear) Flower Extract, Sodium Hyaluronate, Citric Acid, Gluconolactone, Caprylyl Glycol, Sodium Benzoate, Calcium Gluconate, Laminaria Digitata (Kelp) Extract, Saccharomyces Cerevisiae (Yeast) Extract, Orchis Mascula (Orchid) Flower Extract, Phenoxyethanol, Urea, Glucosamine HCl.

PACKAGE LABEL

SeneGence

Microbiome

Defense

Sunscreen Daytime Moisturizer

Broad Spectrum SPF 15

SenePlex+

with Orchid Stem Cells

1.7 fl oz/50 mL